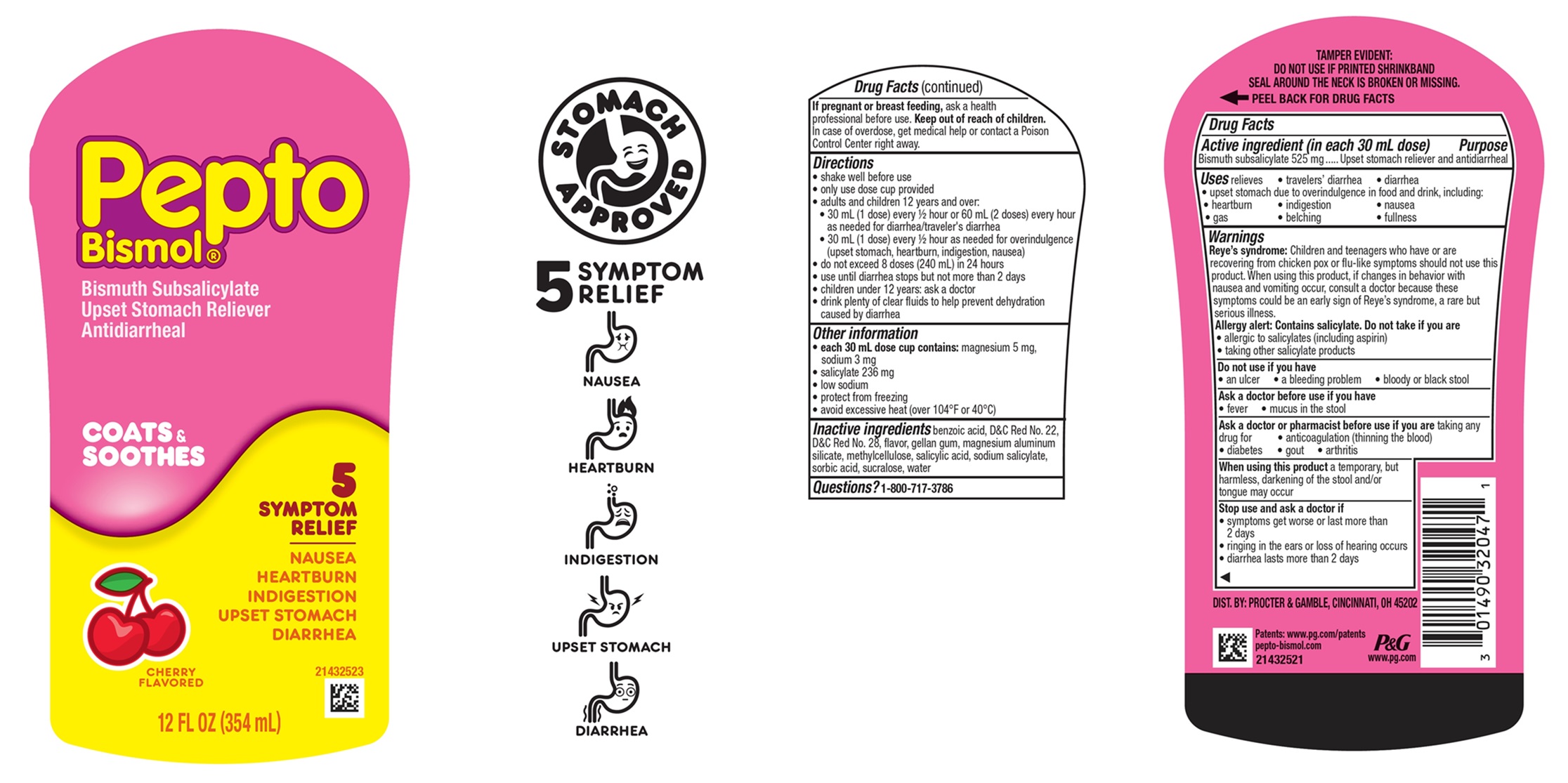 DRUG LABEL: Pepto-Bismol
NDC: 37000-439 | Form: SUSPENSION
Manufacturer: The Procter & Gamble Manufacturing Company
Category: otc | Type: HUMAN OTC DRUG LABEL
Date: 20251218

ACTIVE INGREDIENTS: BISMUTH SUBSALICYLATE 525 mg/30 mL
INACTIVE INGREDIENTS: METHYLCELLULOSE, UNSPECIFIED; BENZOIC ACID; MAGNESIUM ALUMINUM SILICATE; D&C RED NO. 22; D&C RED NO. 28; SUCRALOSE; SALICYLIC ACID; SODIUM SALICYLATE; SORBIC ACID; WATER; GELLAN GUM (HIGH ACYL)

Pepto-Bismol®
Cherry

Drug Facts

Active ingredient (in each 30 mL dose)

Bismuth subsalicylate 525 mg

Purpose

Upset stomach reliever and antidiarrheal

Uses

relieves

- travelers' diarrhea
- diarrhea
- upset stomach due to overindulgence in food and drink, including:
- heartburn
- indigestion
- nausea
- gas
- belching
- fullness

Warnings

Reye's syndrome: Children and teenagers who have or are recovering from chicken pox or flu-like symptoms should not use this product. When using this product, if changes in behavior with nausea and vomiting occur, consult a doctor because these symptoms could be an early sign of Reye's syndrome, a rare but serious illness.

Allergy alert: Contains salicylate. Do not take if you are
• allergic to salicylates (including aspirin)
• taking other salicylate products

Do not use if you have

- an ulcer
- a bleeding problem
- bloody or black stool

Ask a doctor before use if you have

- fever
- mucus in the stool

Ask a doctor or pharmacist before use if you are taking any drug for

- anticoagulation (thinning the blood)
- diabetes
- gout
- arthritis

When using this product

a temporary, but harmless, darkening of the stool and/or tongue may occur

Stop use and ask a doctor if

• symptoms get worse or last more than 2 days
• ringing in the ears or loss of hearing occurs
• diarrhea lasts more than 2 days

PREGNANCY OR BREAST FEEDING

If pregnant or breast-feeding, ask a health professional before use.

Keep out of reach of children.

OVERDOSAGE

In case of overdose, get medical help or contact a Poison Control Center right away.

Directions

- shake well before use
- only use dose cup provided
- adults and children 12 years and over:
- 30 mL (1 dose) every ½ hour or 60 mL (2 doses) every hour as needed for diarrhea/traveler's diarrhea
- 30 mL (1 dose) every ½ hour as needed for overindulgence (upset stomach, heartburn, indigestion, nausea)
- do not exceed 8 doses (240 mL) in 24 hours
- use until diarrhea stops but not more than 2 days
- children under 12 years: ask a doctor
- drink plenty of clear fluids to help prevent dehydration caused by diarrhea

Other information

- each 30 mL dose contains: magnesium 4 mg, sodium 3 mg
- salicylate 236 mg
- low sodium
- protect from freezing
- avoid excessive heat (over 104°F or 40°C)

Inactive ingredients

benzoic acid, D&C Red No. 22, D&C Red No. 28, flavor, gellan gum, magnesium aluminum silicate, methylcellulose, salicylic acid, sodium salicylate, sorbic acid, sucralose, water

Questions?

1-800-717-3786

TAMPER EVIDENT: DO NOT USE IF PRINTED SHRINKBAND SEAL AROUND THE NECK IS BROKEN OR MISSING.

DIST. BY PROCTER & GAMBLE,
CINCINNATI OH 45202

PRINCIPAL DISPLAY PANEL - 354 mL Bottle Label

Pepto

Bismol ®

Bismuth Subsalicylate
Upset Stomach Reliever/
Antidiarrheal

CHERRY
5 SYMPTOM

RELIEF

NAUSEA
HEARTBURN
INDIGESTION
UPSET STOMACH
DIARRHEA

12 FL OZ (354 mL)